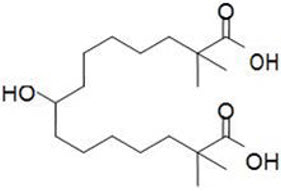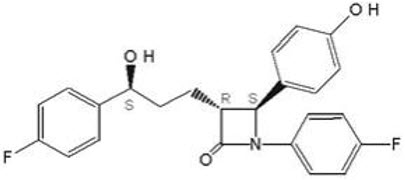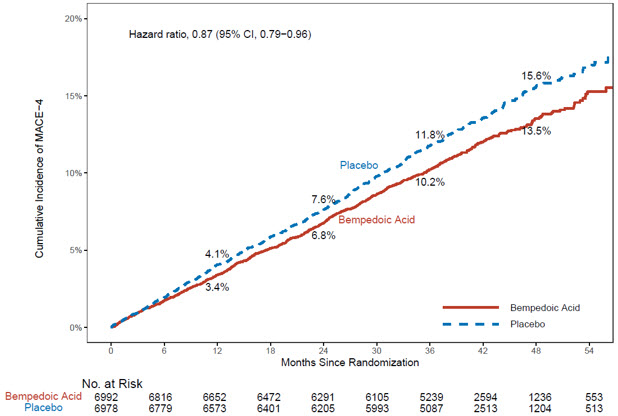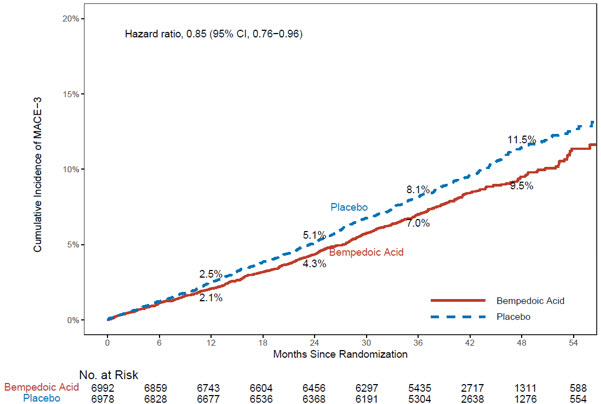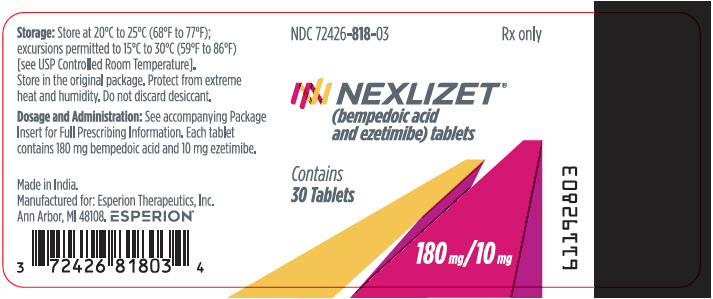 DRUG LABEL: Nexlizet
NDC: 72426-818 | Form: TABLET, FILM COATED
Manufacturer: Esperion Therapeutics, Inc.
Category: prescription | Type: HUMAN PRESCRIPTION DRUG LABEL
Date: 20260115

ACTIVE INGREDIENTS: BEMPEDOIC ACID 180 mg/1 1; EZETIMIBE 10 mg/1 1
INACTIVE INGREDIENTS: LACTOSE MONOHYDRATE; MICROCRYSTALLINE CELLULOSE 102; HYDROXYPROPYL CELLULOSE, UNSPECIFIED; SILICON DIOXIDE; SODIUM STARCH GLYCOLATE TYPE A POTATO; MAGNESIUM STEARATE; POVIDONE K30; SODIUM LAURYL SULFATE; POLYVINYL ALCOHOL, UNSPECIFIED; TITANIUM DIOXIDE; GLYCERYL MONOCAPRYLOCAPRATE; FD&C BLUE NO. 1 ALUMINUM LAKE; FD&C BLUE NO. 2 ALUMINUM LAKE; TALC

HIGHLIGHTS OF PRESCRIBING INFORMATION

These highlights do not include all the information needed to use NEXLIZET® safely and effectively. See full prescribing information for NEXLIZET.
NEXLIZET (bempedoic acid and ezetimibe) tablets, for oral use
Initial U.S. Approval: 2020

RECENT MAJOR CHANGES

Indications and Usage (1) | 11/2025

1 INDICATIONS AND USAGE

NEXLIZET, a combination of bempedoic acid, an adenosine triphosphate citrate lyase (ACL) inhibitor, and ezetimibe, a dietary cholesterol absorption inhibitor, is indicated:

- As an adjunct to diet and exercise to reduce low-density lipoprotein cholesterol (LDL-C) in adults with hypercholesterolemia, including heterozygous familial hypercholesterolemia (HeFH). (1)

Bempedoic acid, a component of NEXLIZET, is indicated:

- To reduce the risk of major adverse cardiovascular events (cardiovascular death, myocardial infarction, stroke, or coronary revascularization) in adults at increased risk for these events who are unable to take recommended statin therapy (including those not taking a statin). (1)

2 DOSAGE AND ADMINISTRATION

- Administer one tablet (180 mg bempedoic acid and 10 mg ezetimibe) orally once daily with or without food. (2.1)
- Swallow the tablet whole. (2.1)
- Coadministration with Bile Acid Sequestrants: Administer at least 2 hours before or at least 4 hours after bile acid sequestrants. (2.2)

3 DOSAGE FORMS AND STRENGTHS

Tablets: 180 mg bempedoic acid/10 mg ezetimibe (3)

4 CONTRAINDICATIONS

Known hypersensitivity to ezetimibe or bempedoic acid or any of the excipients in NEXLIZET. (4, 6.2)

5 WARNINGS AND PRECAUTIONS

Hyperuricemia: Elevations in serum uric acid have occurred. Assess uric acid levels periodically as clinically indicated. Monitor for signs and symptoms of hyperuricemia, and initiate treatment with urate-lowering drugs as appropriate. (5.1)

Tendon Rupture: Tendon rupture has occurred. Discontinue NEXLIZET at the first sign of tendon rupture. Avoid NEXLIZET in patients who have a history of tendon disorders or tendon rupture. (5.2)

6 ADVERSE REACTIONS

- Common adverse reactions with NEXLIZET in the primary hypercholesterolemia trials (incidence ≥ 2% and more frequently than placebo) were upper respiratory tract infection, muscle spasms, hyperuricemia, back pain, abdominal pain or discomfort, bronchitis, pain in extremity, anemia, elevated liver enzymes, diarrhea, arthralgia, sinusitis, fatigue, and influenza. (6.1)
- The common adverse reaction associated with bempedoic acid in the cardiovascular outcomes trial (incidence ≥ 2% and more frequently than placebo) were hyperuricemia, renal impairment, anemia, elevated liver enzymes, muscle spasms, gout, and cholelithiasis. (6.1)

To report SUSPECTED ADVERSE REACTIONS, contact Esperion at 833-377-7633 (833 ESPRMED) or FDA at 1-800-FDA-1088 or www.fda.gov/medwatch.

7 DRUG INTERACTIONS

- Simvastatin: Avoid concomitant use of NEXLIZET with simvastatin greater than 20 mg. (7)
- Pravastatin: Avoid concomitant use of NEXLIZET with pravastatin greater than 40 mg. (7)
- Cyclosporine: Monitor cyclosporine concentrations. (7)
- Fibrates: If cholelithiasis is suspected in a patient receiving NEXLIZET and fenofibrate, consider alternative lipid-lowering therapy. (6.2, 7)
  Concomitant use of NEXLIZET with fibrates may increase triglycerides and decrease high-density lipoprotein cholesterol. (7)

8 USE IN SPECIFIC POPULATIONS

- Pregnancy: Based on mechanism of action, may cause fetal harm. (8.1)

FULL PRESCRIBING INFORMATION

1 INDICATIONS AND USAGE

NEXLIZET, a combination of bempedoic acid and ezetimibe, is indicated:

- as an adjunct to diet and exercise to reduce LDL-C in adults with hypercholesterolemia, including heterozygous familial hypercholesterolemia (HeFH).

Bempedoic acid, a component of NEXLIZET, is indicated:

- to reduce the risk of major adverse cardiovascular events (cardiovascular death, myocardial infarction, stroke, or coronary revascularization) in adults at increased risk for these events who are unable to take recommended statin therapy (including those not taking a statin).

2 DOSAGE AND ADMINISTRATION

2.1 Recommended Dosage and Administration

- The recommended dosage of NEXLIZET is one tablet orally once daily. One tablet of NEXLIZET contains 180 mg of bempedoic acid and 10 mg of ezetimibe.
- Swallow the tablet whole. NEXLIZET can be taken with or without food.
- If a dose is missed, take the missed dose as soon as possible. Do not double the next dose.
- After initiation of NEXLIZET, analyze lipid levels within 8 to 12 weeks.

2.2 Coadministration with Bile Acid Sequestrants

Administer NEXLIZET either at least 2 hours before or at least 4 hours after administration of a bile acid sequestrant [see Drug Interactions (7)].

3 DOSAGE FORMS AND STRENGTHS

NEXLIZET is available as:

- Tablets: 180 mg/10 mg, blue, oval shaped, debossed with "818" on one side and "ESP" on the other side.

4 CONTRAINDICATIONS

NEXLIZET is contraindicated in patients with a prior hypersensitivity to ezetimibe or bempedoic acid or any of the excipients in NEXLIZET [see Adverse Reactions (6.2)]. Serious hypersensitivity reactions, such as anaphylaxis, angioedema, rash and urticaria have been reported with ezetimibe or bempedoic acid.

5 WARNINGS AND PRECAUTIONS

5.1 Hyperuricemia

Bempedoic acid, a component of NEXLIZET, inhibits renal tubular OAT2 and may increase blood uric acid levels [see Clinical Pharmacology (12.3)]. In the primary hypercholesterolemia trials [see Clinical Studies (14.1)], 26% of bempedoic acid-treated patients with normal baseline uric acid values (versus 9.5% placebo) experienced hyperuricemia one or more times, and 3.5% of patients experienced clinically significant hyperuricemia reported as an adverse reaction (versus 1.1% placebo). Increases in uric acid levels usually occurred within the first 4 weeks of treatment initiation, persisted throughout treatment, and returned to baseline following discontinuation of treatment. After 12 weeks of treatment, the mean placebo-adjusted increase in uric acid compared to baseline was 0.8 mg/dL for patients treated with bempedoic acid. In the cardiovascular outcomes trial [see Clinical Studies (14.2)], 16.4% of bempedoic acid-treated patients experienced clinically significant hyperuricemia reported as an adverse reaction (versus 8.2% placebo).

Elevated blood uric acid may lead to the development of gout. In the primary hypercholesterolemia trials, gout was reported in 1.5% of patients treated with bempedoic acid versus 0.4% of patients treated with placebo. In the cardiovascular outcomes trial, gout was reported in 3.2% of patients treated with bempedoic acid and 2.2% treated with placebo.

Advise patients to contact their healthcare provider if symptoms of hyperuricemia occur. Assess serum uric acid when clinically indicated. Monitor patients for signs and symptoms of hyperuricemia, and initiate treatment with urate-lowering drugs as appropriate.

5.2 Tendon Rupture

Bempedoic acid, a component of NEXLIZET, is associated with an increased risk of tendon rupture or injury. In the primary hypercholesterolemia trials [see Clinical Studies (14.1)], tendon rupture occurred in 0.5% of patients treated with bempedoic acid versus 0% of placebo-treated patients and involved the rotator cuff (the shoulder), biceps tendon, or Achilles tendon. Tendon rupture occurred within weeks to months of starting bempedoic acid. In the cardiovascular outcomes trial [see Clinical Studies (14.2)], tendon rupture events occurred in 1.2% of bempedoic acid-treated patients versus 0.9% of placebo-treated patients. Tendon rupture may occur more frequently in patients over 60 years of age, in those taking corticosteroid or fluoroquinolone drugs, in patients with renal failure, and in patients with previous tendon disorders.

Discontinue NEXLIZET immediately if the patient experiences rupture of a tendon. Consider discontinuing NEXLIZET if the patient experiences joint pain, swelling, or inflammation. Advise patients to rest at the first sign of tendinitis or tendon rupture and to contact their healthcare provider if tendinitis or tendon rupture symptoms occur. Consider alternative therapy in patients with a history of tendon disorders or tendon rupture.

6 ADVERSE REACTIONS

The following clinically significant adverse reactions are described elsewhere in the labeling:

- Hyperuricemia [see Warnings and Precautions (5.1)]
- Tendon Rupture [see Warnings and Precautions (5.2)]

6.1 Clinical Trials Experience

Because clinical trials are conducted under widely varying conditions, adverse reaction rates observed in the clinical trials of a drug cannot be directly compared to rates in the clinical trials of another drug and may not reflect the rates observed in clinical practice.

Bempedoic acid

The data in Table 1 reflect exposure to bempedoic acid in two placebo-controlled primary hypercholesterolemia trials that included 2,009 patients treated with bempedoic acid for 52 weeks (median treatment duration of 52 weeks) [see Clinical Studies (14.1)]. The mean age for bempedoic acid-treated patients was 65 years, 29% were female, 95% were White, 3% were Black or African American, 1% were Asian, and 1% were other races; 3% identified as Hispanic or Latino ethnicity. All patients received bempedoic acid 180 mg orally once daily plus maximally tolerated statin therapy alone or in combination with other lipid-lowering therapies. At baseline, 97% of patients had CVD and about 4% had a diagnosis of HeFH. Patients on simvastatin 40 mg/day or higher were excluded from the trials.

In the primary hypercholesterolemia trials, adverse reactions led to discontinuation of treatment in 11% of bempedoic acid-treated patients and 8% of placebo-treated patients. The most common reasons for bempedoic acid treatment discontinuation were muscle spasms (0.5% versus 0.3% placebo), diarrhea (0.4% versus 0.1% placebo), and pain in extremity (0.3% versus 0.0% placebo). Adverse reactions reported in at least 2% of bempedoic acid-treated patients and more frequently than in placebo-treated patients are shown in Table 1.

Table 1. Adverse Reactions (≥ 2% and greater than placebo) in Bempedoic Acid-Treated Patients with Primary Hypercholesterolemia and CVD or HeFH (Trials 2 and 3)
Adverse Reaction | Placebo [Background therapy included statin ± other lipid-lowering therapies] (N = 999) % | Bempedoic acid (N = 2,009) %
Upper respiratory tract infection | 4.0 | 4.5
Muscle spasms | 2.3 | 3.6
Hyperuricemia [Grouped term that includes other related terms] | 1.1 | 3.5
Back pain | 2.2 | 3.3
Abdominal pain or discomfort | 2.2 | 3.1
Bronchitis | 2.5 | 3.0
Pain in extremity | 1.7 | 3.0
Anemia | 1.9 | 2.8
Elevated liver enzymes | 0.8 | 2.1

In the cardiovascular outcomes trial in which 7,001 patients were exposed to bempedoic acid and 6,964 patients were exposed to placebo for a median of 3.1 years [see Clinical Studies (14.2)], adverse reactions led to discontinuation of treatment in 11% of bempedoic acid-treated patients and 10% of placebo-treated patients. Adverse reactions reported in at least 2% of bempedoic acid-treated patients and more frequently than placebo are shown in Table 2.

Table 2. Adverse Reactions (≥ 2% and 0.5% greater than placebo) in Bempedoic Acid-Treated Patients with CVD or at High Risk for CVD (Trial 4)
Adverse Reaction | Placebo (N=6,964) % | Bempedoic Acid (N=7,001) %
Hyperuricemia [Grouped term that includes other related terms] | 8 | 16
Renal impairment [Renal impairment includes laboratory related terms including glomerular filtration rate decreased, blood creatinine increased and hematuria] | 9 | 11
Anemia | 4 | 5
Elevated liver enzymes | 3 | 4
Muscle spasms | 3 | 4
Gout | 2 | 3
Cholelithiasis | 1 | 2

Other Adverse Reactions

Tendon Rupture

In the hypercholesterolemia trials, tendon rupture occurred in 0.5% of bempedoic acid-treated patients versus 0% of placebo-treated patients. In the cardiovascular outcomes trial, tendon rupture events occurred in 1.2% of bempedoic acid-treated patients versus 0.9% of placebo-treated patients.

Gout

In the hypercholesterolemia trials, gout occurred in 1.5% of bempedoic acid-treated patients versus 0.4% of placebo-treated patients. In the cardiovascular outcomes trial, gout occurred in 3.2% of bempedoic acid-treated patients versus 2.2% of placebo-treated patients.

Laboratory Tests

Bempedoic acid was associated with persistent changes in multiple laboratory tests that occurred within the first 4 weeks of treatment, and returned to baseline following discontinuation of treatment.

Increase in Creatinine and Blood Urea Nitrogen

In the hypercholesterolemia trials, there was a mean increase in serum creatinine of 0.05 mg/dL compared to baseline with bempedoic acid at Week 12. Approximately 3.8% of patients treated with bempedoic acid had blood urea nitrogen values that doubled (versus 1.5% placebo), and about 2.2% of patients had creatinine values that increased by 0.5 mg/dL (versus 1.1% placebo). In the cardiovascular outcomes trial, 7.1% of patients had creatinine values that increased by 0.5 mg/dL (versus 5.5% placebo) and 9.5% of patients in the bempedoic acid group had BUN values that increased ≥ 2× baseline (versus 6.2% placebo).

Decrease in Hemoglobin and Leukocytes

In the hypercholesterolemia trials, approximately 5.1% of patients treated with bempedoic acid (versus 2.3% placebo) had decreases in hemoglobin levels of 2 or more g/dL and below the lower limit of normal on one or more occasion. Anemia was reported in 2.8% of patients treated with bempedoic acid and 1.9% of patients treated with placebo. Approximately 9.0% of bempedoic acid-treated patients with normal baseline leukocyte count had a decrease to less than the lower limit of normal on one or more occasion (versus 6.7% placebo). Leukocyte decrease was generally asymptomatic and did not require medical intervention. In the hypercholesterolemia trials, there was a small imbalance in skin or soft tissue infections, including cellulitis (0.8% versus 0.4%), but there was no imbalance in other infections.

In the cardiovascular outcomes trial, 10.8% of patients (versus 7.4% placebo) had a decrease in hemoglobin of 2 or more g/dL and below the lower limit of normal. Anemia was reported in 4.7% of patients treated with bempedoic acid and 3.9% of patients treated with placebo. There were 9.3% of bempedoic acid-treated patients with a leukocyte count below the lower limit of normal (and normal at baseline) at any point (versus 6.8% placebo).

Increase in Platelet Count

In the hypercholesterolemia trials, approximately 10.1% of bempedoic acid-treated patients (versus 4.7% placebo) had increases in platelet counts of 100× 10^9/L or more on one or more occasion. In the cardiovascular outcomes trial, 18.6% of patients in the bempedoic acid-treated group (versus 10.2% placebo) had an increase in platelet count of 100 × 10^9/L or more. Platelet count increase was asymptomatic and did not result in increased risk for thromboembolic events.

Increase in Liver Enzymes

In the hypercholesterolemia trials, increases in hepatic transaminases (AST and/or ALT) were observed with bempedoic acid. In most cases, the elevations were transient and resolved or improved with continued therapy or after discontinuation of therapy. Increases to more than 3× the upper limit of normal (ULN) in AST occurred in 1.4% of patients treated with bempedoic acid versus 0.4% of placebo patients, and increases to more than 5× ULN occurred in 0.4% of bempedoic acid- treated versus 0.2% of placebo-treated patients. Increases in ALT occurred with similar incidence between bempedoic acid- and placebo-treated patients. Elevations in transaminases were generally asymptomatic and not associated with elevations ≥ 2× ULN in bilirubin or with cholestasis.

In the cardiovascular outcomes trial, the incidence of repeated and confirmed ALT and/or AST >3× ULN was 1.6% in the bempedoic acid-treated group (versus 1.0% placebo). A higher percentage of patients in the bempedoic acid-treated group had hepatic enzyme elevations versus placebo (4.5% versus 3.0%, respectively).

Increase in Creatine Kinase

In the hypercholesterolemia trials, approximately 1.0% of patients (versus 0.6% placebo) had elevations of CK levels of 5 or more times the normal value on one or more occasions, and 0.4% of patients (versus 0.2% placebo) had elevations of CK levels of 10 or more times.

Ezetimibe

In 10 double-blind, placebo-controlled clinical trials [see Clinical Studies (14.1)], 2,396 patients with primary hypercholesterolemia (age range 9 to 86 years, 50% were female, 90% were White, 5% were Black or African American, 2% were Asian, 3% other races; 3% identified as Hispanic or Latino ethnicity) and elevated LDL-C were treated with ezetimibe 10 mg/day for a median treatment duration of 12 weeks (range 0 to 39 weeks).

Adverse reactions reported in ≥ 2% of patients treated with ezetimibe and at an incidence greater than placebo in placebo-controlled studies of ezetimibe are shown in Table 3.

Table 3. Adverse Reactions Occurring in ≥ 2% and greater than placebo in Ezetimibe-treated Patients
Adverse Reaction | Placebo (%) N = 1,159 | Ezetimibe 10 mg (%) N = 2,396
Upper respiratory tract infection | 2.5 | 4.3
Diarrhea | 3.7 | 4.1
Arthralgia | 2.2 | 3.0
Sinusitis | 2.2 | 2.8
Pain in extremity | 2.5 | 2.7
Fatigue | 1.5 | 2.4
Influenza | 1.5 | 2.0

NEXLIZET

In a 4-arm, 12-week, randomized, double-blind, placebo-controlled, parallel group, factorial trial, 85 patients received NEXLIZET (180 mg of bempedoic acid and 10 mg of ezetimibe) once daily [see Clinical Studies (14.1)]. The mean age for NEXLIZET-treated patients was 62 years, 51% were female, 78% were White, 19% were Black or African American, 2% were Asian, and 1% were American Indian or Alaska Native; 11% identified as Hispanic or Latino ethnicity. At baseline, 61% of patients had CVD and/or a diagnosis of HeFH. All patients received NEXLIZET plus maximally tolerated statin therapy. Patients taking simvastatin 40 mg/day or higher and patients taking non-statin lipid-lowering therapy (including fibrates, niacin, bile acid sequestrants, ezetimibe, and PCSK9 inhibitors) were excluded from the trial.

Adverse reactions led to discontinuation of treatment in 8% of patients on NEXLIZET, 5% of patients on placebo, 10% of patients on bempedoic acid, and 12% of patients on ezetimibe. The most common reason for NEXLIZET treatment discontinuation was oral discomfort (2% NEXLIZET versus 0% placebo). The most commonly reported adverse reactions (incidence ≥ 3% and greater than placebo) observed with NEXLIZET, but not observed in clinical trials of bempedoic acid or ezetimibe, were urinary tract infection (5.9% NEXLIZET versus 2.4% placebo), nasopharyngitis (4.7% NEXLIZET versus 0% placebo), and constipation (4.7% NEXLIZET versus 0% placebo).

6.2 Postmarketing Experience

The following adverse reactions have been identified during post approval use of ezetimibe and/or bempedoic acid. Because these reactions are reported voluntarily from a population of uncertain size, it is not always possible to reliably estimate their frequency or establish a causal relationship to drug exposure.

Blood Disorders: thrombocytopenia

Gastrointestinal Disorders: abdominal pain; pancreatitis; nausea

Hepatobiliary Disorders: elevations in liver transaminases, including elevations more than 5× ULN; hepatitis; cholelithiasis; cholecystitis

Immune System Disorders: Hypersensitivity reactions including: anaphylaxis, angioedema, wheezing, rash, and urticaria

Musculoskeletal Disorders: elevated creatine phosphokinase; myopathy/rhabdomyolysis

Nervous System Disorders: dizziness; paresthesia; depression; headache

Skin and Subcutaneous Tissue Disorders: erythema multiforme

7 DRUG INTERACTIONS

No specific pharmacokinetic drug interaction studies with NEXLIZET have been conducted. Table 4 lists drug interactions with NEXLIZET that have been identified in studies with bempedoic acid or ezetimibe.

Table 4. Clinically Important Drug Interactions with NEXLIZET
Simvastatin
Clinical Impact: | Concomitant use of NEXLIZET with simvastatin causes an increase in simvastatin concentration and may increase the risk of simvastatin-related myopathy [see Clinical Pharmacology (12.3)].
Intervention: | Avoid concomitant use of NEXLIZET with simvastatin greater than 20 mg.
Pravastatin
Clinical Impact: | Concomitant use of NEXLIZET with pravastatin causes an increase in pravastatin concentration and may increase the risk of pravastatin-related myopathy [see Clinical Pharmacology (12.3)].
Intervention: | Avoid concomitant use of NEXLIZET with pravastatin greater than 40 mg.
Cyclosporine
Clinical Impact: | Concomitant use of NEXLIZET and cyclosporine increases ezetimibe and cyclosporine concentrations. The degree of increase in ezetimibe exposure may be greater in patients with severe renal insufficiency [see Clinical Pharmacology (12.3)].
Intervention: | Monitor cyclosporine concentrations in patients receiving NEXLIZET and cyclosporine. In patients treated with cyclosporine, weigh the potential effects of the increased exposure to ezetimibe from concomitant use against the benefits of alterations in lipid levels provided by NEXLIZET.
Fibrates
Clinical Impact: | Both fenofibrate and ezetimibe (a component of NEXLIZET) may increase cholesterol excretion into the bile, leading to cholelithiasis. Coadministration of NEXLIZET with fibrates other than fenofibrate is not recommended [see Adverse Reactions (6.1)].
Intervention: | If cholelithiasis is suspected in a patient receiving NEXLIZET and fenofibrate, gallbladder studies are indicated and alternative lipid-lowering therapy should be considered.
Clinical Impact: | Concomitant administration of fibrates with bempedoic acid (a component of NEXLIZET) resulted in increased triglycerides and decreased high-density lipoprotein cholesterol (HDL-C) in some patients in clinical studies and post-marketing reports. Reversibility of both increased triglycerides and decreased HDL-C levels was observed when either bempedoic acid or fibrate therapy was discontinued.
Intervention: | Monitor triglycerides and HDL-C four weeks after initial concomitant use of NEXLIZET and a fibrate and periodically thereafter. If increased triglycerides or decreased HDL-C levels are detected, discontinue NEXLIZET or fibrate therapy based on clinical judgment. Monitor triglycerides and HDL-C levels until levels return to baseline.
Cholestyramine
Clinical Impact: | Concomitant use of NEXLIZET and cholestyramine decreases ezetimibe concentration. This may result in a reduction of efficacy [see Clinical Pharmacology (12.3)].
Intervention: | Administer NEXLIZET either at least 2 hours before or at least 4 hours after bile acid sequestrants [see Dosage and Administration (2.2)].

8 USE IN SPECIFIC POPULATIONS

8.1 Pregnancy

Risk Summary

Discontinue NEXLIZET when pregnancy is recognized unless the benefits of therapy outweigh the potential risks to the fetus.

There are insufficient data on bempedoic acid use in pregnant women to evaluate for a drug-associated risk of major birth defects, miscarriage, or adverse maternal or fetal outcomes. There are insufficient data on ezetimibe use in pregnant women to evaluate for a drug-associated risk of major birth defects, miscarriage, or adverse maternal or fetal outcomes. In animal reproduction studies, bempedoic acid was not teratogenic in rats and rabbits when administered at doses resulting in exposures up to 11 and 12 times, respectively, the human exposures at the maximum clinical dose, based on AUC. In oral (gavage) embryo-fetal development studies of ezetimibe conducted in rats and rabbits during organogenesis, there was no evidence of maternal toxicity or embryo-fetal teratogenic or toxicologic effects at exposures up to 10 and 150 times the human exposure, respectively, based on AUC (see Data). NEXLIZET decreases cholesterol synthesis and possibly the synthesis of other biologically active substances derived from cholesterol; therefore, NEXLIZET may cause fetal harm when administered to pregnant women based on the mechanism of action [see Clinical Pharmacology (12.1)]. In addition, treatment of hypercholesterolemia is not generally necessary during pregnancy. Atherosclerosis is a chronic process and the discontinuation of lipid-lowering drugs during pregnancy should have little impact on the outcome of long-term therapy of primary hypercholesterolemia for most patients.

The estimated background risk of major birth defects and miscarriage for the indicated population is unknown. In the U.S. general population, the estimated background risk of major birth defects and miscarriage in clinically recognized pregnancies is 2-4% and 15-20%, respectively.

Report pregnancies to the Esperion Therapeutics, Inc. Adverse Event reporting line at 1-833-377-7633.

Data

Animal Data

Bempedoic acid

Bempedoic acid was not teratogenic when given orally at doses of 60 and 80 mg/kg/day, resulting in 11 and 12 times the systemic exposure in humans at the maximum recommended human dose (MRHD) of 180 mg to pregnant rats and rabbits, respectively. In an embryofetal development study in rats, bempedoic acid was given orally to pregnant rats at 10, 30, and 60 mg/kg/day during the period of organogenesis from gestation day 6 to 17. There were increases in the incidence of non-adverse fetal skeletal variations (bent long bones and bent scapula and incomplete ossification) at doses ≥ 10 mg/kg/day (less than the clinical exposure) in the absence of maternal toxicity. At maternally toxic doses, bempedoic acid caused decreases in the numbers of viable fetuses, increases in post-implantation loss, and increased total resorptions at 60 mg/kg/day (11 times MRHD) and reduced fetal body weight at ≥ 30 mg/kg/day (4 times the MRHD). No adverse development effects were observed when bempedoic acid was given to pregnant rabbits during the period of organogenesis (gestation day 6 to 18) at doses up to 80 mg/kg/day (12 times MRHD).

In a pre- and post-natal development study in pregnant rats given oral doses of bempedoic acid at 5, 10, 20, 30 and 60 mg/kg/day throughout pregnancy and lactation (gestation day 6 to lactation day 20), there were adverse effects on delivery in the presence of maternal toxicity, including: increases in stillborn pups, reductions in numbers of live pups, pup survival, pup growth and slight delays in learning and memory at ≥ 10 mg/kg/day (at exposures equivalent to the MRHD).

Ezetimibe

In oral (gavage) embryo-fetal development studies of ezetimibe conducted in rats (gestation days 6-15) and rabbits (gestation days 7-19), there was no evidence of maternal toxicity or embryolethal effects at the doses tested (250, 500, 1,000 mg/kg/day). In rats, increased incidences of common fetal skeletal findings (extra pair of thoracic ribs, unossified cervical vertebral centra, shortened ribs) were observed at 1,000 mg/kg/day (approximately 10 times the human exposure at 10 mg daily based on AUC0-24hr for total ezetimibe). In rabbits treated with ezetimibe, an increased incidence of extra thoracic ribs was observed at 1,000 mg/kg/day (150 times the human exposure at 10 mg daily based on AUC0-24hr for total ezetimibe). The animal-to-human exposure multiple for total ezetimibe at the no-observed effect level was 6 times for rat and 134 times for rabbit.

Fetal exposure to ezetimibe (conjugated and unconjugated) was confirmed in subsequent placental transfer studies conducted using a maternal dose of 1,000 mg/kg/day. The fetal maternal plasma exposure ratio (total ezetimibe) was 1.5 for rats on gestation day 20 and 0.03 for rabbits on gestation day 22.

The effect of ezetimibe on prenatal and postnatal development and maternal function was evaluated in pregnant rats at doses of 100, 300 or 1,000 mg/kg/day from gestation day 6 through lactation day 21. No maternal toxicity or adverse developmental outcomes were observed up to and including the highest dose tested (17 times the human exposure at 10 mg daily based on AUC0-24hr for total ezetimibe).

Multiple-dose studies of ezetimibe given in combination with statins in rats and rabbits during organogenesis resulted in higher ezetimibe and statin exposures. Reproductive findings occurred at lower doses in combination therapy compared to monotherapy.

Bempedoic acid/ezetimibe fixed combination drug product (FCDP)

In a combination embryofetal development study in rats, bempedoic acid and ezetimibe were given orally at 4 and 112-times MRHD (based on AUC) during the period of organogenesis (gestation day 6 to 17) in pregnant rats. Bempedoic acid in combination with ezetimibe did not alter the effects on embryo-fetal development profile of bempedoic acid or ezetimibe.

8.2 Lactation

Risk Summary

Bempedoic acid and ezetimibe have been detected in breast milk of lactating women who received six consecutive daily doses of 180 mg bempedoic acid plus 10 mg of ezetimibe administered as a single tablet. The mean daily infant dose through breastmilk was approximately 0.03 mg/day (95% CI: 0.01; 0.06) for bempedoic acid and 0.0002 mg/day (95% CI: 0.0001; 0.0003) for ezetimibe. A mean calculated daily infant oral dosage was 0.0109 mg/kg/day for bempedoic acid and 0.0001 mg/kg/day for ezetimibe, based on a standard infant milk intake of 150 mL/kg/day. The mean (SD) relative infant dose (RID) was approximately 0.5 (0.29)% for bempedoic acid and 0.04 (0.01)% for ezetimibe of the corresponding maternal weight-adjusted dosages (see Data). Concentrations of ESP15228, the active metabolite of bempedoic acid, in breast milk were below the limit of quantitation (20 ng/mL) in 7 of 8 subjects studied. Mean amounts of 0.0010 mg ezetimibe-glucuronide, the active metabolite of ezetimibe, were recovered in breast milk during the 24 hours following the final 180 mg/10 mg maternal dose. There is no information regarding the effects of NEXLIZET on the breastfed infant, or the effects on milk production.

NEXLIZET decreases cholesterol synthesis and possibly the synthesis of other biologically active substances derived from cholesterol and may cause harm to the breastfed infant. The developmental and health benefits of breastfeeding should be considered along with the mother's clinical need for NEXLIZET and any potential adverse effects on the breastfed infant from NEXLIZET or from the underlying maternal condition [see Clinical Pharmacology (12.1)].

Data

A lactation study in 8 healthy lactating women evaluated the concentrations of bempedoic acid and ezetimibe in mature breast milk. NEXLIZET 180 mg/10 mg oral tablet was given once daily for six consecutive days. The geometric mean estimates of bempedoic acid and ezetimibe Cmax in breast milk were 107.5 ng/mL (range: 56 to 234 ng/mL) and 0.630 ng/mL (range: 0.300 to 1.1 ng/mL), respectively. Maximum bempedoic acid and ezetimibe excretion occurred within 3 hours after dosing.

8.4 Pediatric Use

The safety and effectiveness of NEXLIZET have not been established in pediatric patients.

8.5 Geriatric Use

Of the 301 patients in the clinical trial of NEXLIZET, 149 (50%) were 65 years of age and older, while 49 (16%) were 75 years of age and over. No overall differences in safety or effectiveness of NEXLIZET have been observed between patients 65 years of age and older and younger adult patients.

8.7 Hepatic Impairment

No dosage adjustment is necessary in patients with mild hepatic impairment (Child-Pugh A) [see Clinical Pharmacology (12.3)]. NEXLIZET is not recommended in patients with moderate or severe hepatic impairment (Child-Pugh B or C) due to the unknown effects of the increased exposure to ezetimibe [see Clinical Pharmacology (12.3)].

10 OVERDOSAGE

There is no clinical experience with NEXLIZET overdosage. In the event of an overdosage, consider contacting the Poison Help line (1-800-222-1222) or a medical toxicologist for additional overdosage management recommendations.

11 DESCRIPTION

NEXLIZET tablets, for oral use, contain bempedoic acid, an adenosine triphosphate-citrate lyase (ACL) inhibitor, and ezetimibe, a dietary cholesterol absorption inhibitor.

The chemical name for bempedoic acid is 8-hydroxy-2,2,14,14-tetramethyl-pentadecanedioic acid. The molecular formula is C19H36O5, and the molecular weight is 344.5 grams per mole. Bempedoic acid is a white to off-white crystalline powder that is highly soluble in ethanol, isopropanol and pH 8.0 phosphate buffer, and insoluble in water and aqueous solutions below pH 5.

Structural formula:

The chemical name for ezetimibe is 1-(4-fluorophenyl)-3(R)-[3-(4-fluorophenyl)-3(S)- hydroxypropyl]-4(S)-(4-hydroxyphenyl)-2-azetidinone. The molecular formula is C24H21F2NO3 and the molecular weight is 409.4 grams per mole. Ezetimibe is a white, crystalline powder that is freely to very soluble in ethanol, methanol, and acetone and practically insoluble in water.

Structural formula:

Each film-coated tablet of NEXLIZET contains 180 mg of bempedoic acid and 10 mg of ezetimibe, and the following inactive ingredients: colloidal silicon dioxide, hydroxy propyl cellulose, lactose monohydrate, magnesium stearate, microcrystalline cellulose, povidone K30, sodium lauryl sulfate, sodium starch glycolate. The film coating comprises of FD&C Blue #1/Brilliant Blue FCF Aluminum Lake, FD&C Blue #2/Indigo Carmine Aluminum Lake, glyceryl monocaprylocaprate, partially hydrolyzed polyvinyl alcohol, sodium lauryl sulfate, talc, and titanium dioxide.

12 CLINICAL PHARMACOLOGY

12.1 Mechanism of Action

NEXLIZET contains bempedoic acid and ezetimibe. NEXLIZET reduces elevated LDL-C through inhibition of cholesterol synthesis in the liver and absorption in the intestine.

Bempedoic acid

Bempedoic acid is an adenosine triphosphate-citrate lyase (ACL) inhibitor that lowers LDL-C by inhibition of cholesterol synthesis in the liver. ACL is an enzyme upstream of 3-hydroxy-3-methyl-glutaryl-coenzyme A (HMG-CoA) reductase in the cholesterol biosynthesis pathway. Bempedoic acid and its active metabolite, ESP15228, require coenzyme A (CoA) activation by very long-chain acyl-CoA synthetase 1 (ACSVL1) to ETC-1002-CoA and ESP15228-CoA, respectively. ACSVL1 is expressed primarily in the liver. Inhibition of ACL by ETC-1002-CoA results in decreased cholesterol synthesis in the liver and lowers LDL-C in blood via upregulation of low-density lipoprotein receptors.

Ezetimibe

Ezetimibe reduces blood cholesterol by inhibiting the absorption of cholesterol by the small intestine. The molecular target of ezetimibe has been shown to be the sterol transporter, Niemann-Pick C1-Like 1 (NPC1L1), which is involved in the intestinal uptake of cholesterol and phytosterols. Ezetimibe localizes at the brush border of the small intestine and inhibits the absorption of cholesterol, leading to a decrease in the delivery of intestinal cholesterol to the liver. This causes a reduction of hepatic cholesterol stores and an increase in LDL receptors, resulting in clearance of cholesterol from the blood.

12.2 Pharmacodynamics

Administration of bempedoic acid and ezetimibe in combination with other lipid modifying agents, decreases LDL-C, non-high density lipoprotein cholesterol (non-HDL-C), apolipoprotein B (apo B), and total cholesterol (TC) in patients with hypercholesterolemia.

Cardiac Electrophysiology

At a dose of 240 mg (1.3 times the approved recommended dose), bempedoic acid does not prolong the QT interval to any clinically relevant extent.

The effect of ezetimibe or NEXLIZET on QT interval has not been evaluated.

12.3 Pharmacokinetics

Absorption

NEXLIZET

The bioavailability of NEXLIZET tablets was similar relative to that from the individual tablets, coadministered. Maximum plasma concentration (Cmax) values for bempedoic acid and its active metabolite (ESP15228) were similar between formulations, but ezetimibe glucuronide and ezetimibe Cmax values were approximately 22% and 13% lower, respectively, for NEXLIZET relative to the individual tablets, coadministered. Given a similar overall extent of ezetimibe glucuronide and ezetimibe exposure (as measured by AUC), a 22% lower Cmax is unlikely to be clinically significant.

Bempedoic acid

Following single oral administration of NEXLIZET (180 mg of bempedoic acid and 10 mg of ezetimibe), mean (± SD) Cmax and AUC of bempedoic acid were 12.6 (± 2.80) µg/mL and 202 (± 43.4) µg.hr/mL, respectively; the median time to maximum concentration (Tmax) was 3.0 hours. Following multiple-dose administration of bempedoic acid monotherapy, the steady-state maximum plasma concentration (Cmax) and AUC at 180 mg/day were 20.6 ± 6.1 µg/mL and 289.0 ± 96.4 µg∙h/mL, respectively. Bempedoic acid steady-state pharmacokinetics were generally linear over a range of >60 mg to 220 mg (approximately 33% to 122% of the recommended dosage of 180 mg daily). There were no time-dependent changes in bempedoic acid pharmacokinetics following repeat administration at the recommended dosage, and bempedoic acid steady-state was achieved after 7 days. The mean accumulation ratio was approximately 2.3-fold.

The steady-state Cmax and AUC of the active metabolite (ESP15228) of bempedoic acid were 2.8 ± 0.9 µg/mL and 51.2 ± 17.2 µg∙h/mL, respectively. ESP15228 likely made a minor contribution to the overall clinical activity of bempedoic acid based on systemic exposure, relative potency, and pharmacokinetic properties.

Ezetimibe

After a single dose of NEXLIZET to fasted adults, mean ± SD ezetimibe Cmax of 3.56 ± 1.90 ng/mL were attained with a median Tmax of 5 hr. Ezetimibe-glucuronide mean Cmax values of 107 ± 46 ng/mL were achieved with a median Tmax of 1 hr. For ezetimibe monotherapy, there was no substantial deviation from dose proportionality between 5 mg and 20 mg (0.5- to 2-fold the recommended dosage). The absolute bioavailability of ezetimibe cannot be determined, as the compound is virtually insoluble in aqueous media suitable for injection.

Effect of Food

NEXLIZET

After the administration of NEXLIZET with a high-fat, high calorie breakfast in healthy subjects, the AUC for bempedoic acid and ezetimibe were comparable to the fasted state. Compared to the fasted state, the fed state resulted in 30% and 12% reductions in Cmax and 2-hour and 2.5-hour delays in median time to attain maximum concentration (Tmax) of bempedoic acid and ezetimibe, respectively. For ezetimibe glucuronide, a 12% and 42% decrease in AUC and Cmax, respectively, were observed under fed relative to fasted conditions.

This effect of food is not considered to be clinically meaningful.

Distribution

Bempedoic acid

The bempedoic acid apparent volume of distribution (V/F) was 18 L. Plasma protein binding of bempedoic acid, its glucuronide and its active metabolite, ESP15228, were 99.3%, 98.8% and 99.2%, respectively. Bempedoic acid does not partition into blood cells.

Ezetimibe

Ezetimibe and ezetimibe-glucuronide are highly bound (>90%) to human plasma proteins.

Elimination

Bempedoic acid

The steady-state clearance (CL/F) of bempedoic acid was 11.2 mL/min after once-daily dosing; renal clearance of unchanged bempedoic acid represented less than 2% of total clearance. The mean ± SD half-life for bempedoic acid in humans was 21 ± 11 hours at steady-state.

Ezetimibe

Both ezetimibe and ezetimibe-glucuronide are eliminated from plasma with a half-life of approximately 22 hours for both.

Metabolism

Bempedoic acid

The primary route of elimination for bempedoic acid is through metabolism to the acyl glucuronide. Bempedoic acid is also reversibly converted to an active metabolite (ESP15228) based on aldo-keto reductase activity observed in vitro from human liver. Mean plasma AUC metabolite/parent drug ratio for ESP15228 following repeat-dose administration was 18% and remained constant over time. Both bempedoic acid and ESP15228 are converted to inactive glucuronide conjugates in vitro by UGT2B7. Bempedoic acid, ESP15228 and their respective conjugated forms were detected in plasma with bempedoic acid accounting for the majority (46%) of the AUC0-48h and its glucuronide being the next most prevalent (30%). ESP15228 and its glucuronide represented 10% and 11% of the plasma AUC0-48h, respectively.

Ezetimibe

Ezetimibe is primarily metabolized in the small intestine and liver via glucuronide conjugation with subsequent biliary and renal excretion. Minimal oxidative metabolism has been observed in all species evaluated.

In humans, ezetimibe is rapidly metabolized to ezetimibe-glucuronide. Ezetimibe and ezetimibe- glucuronide are the major drug-derived compounds detected in plasma, constituting approximately 10% to 20% and 80% to 90% of the total drug in plasma, respectively. Plasma concentration-time profiles exhibit multiple peaks, suggesting enterohepatic recycling.

Excretion

Bempedoic acid

Following single oral administration of 240 mg of bempedoic acid (1.3 times the approved recommended dose), approximately 70% of the total dose (bempedoic acid and its metabolites) was recovered in urine, primarily as the acyl glucuronide conjugate of bempedoic acid, and approximately 30% was recovered in feces. Less than 5% of the administered dose was excreted as unchanged bempedoic acid in feces and urine combined.

Ezetimibe

Following oral administration of 14C-ezetimibe (20 mg) to human subjects, total ezetimibe (ezetimibe + ezetimibe-glucuronide) accounted for approximately 93% of the total radioactivity in plasma. Approximately 78% and 11% of the administered radioactivity were recovered in the feces and urine, respectively, over a 10-day collection period. After 48 hours, there were no detectable levels of radioactivity in the plasma.

Ezetimibe was the major component in feces, and accounted for 69% of the administered dose, while ezetimibe-glucuronide was the major component in urine and accounted for 9% of the administered dose.

Specific Populations

Patients with Renal Impairment

Bempedoic acid

No clinically significant differences in the pharmacokinetics of bempedoic acid were observed in subjects with renal impairment (mild, moderate, and severe renal impairment or renal failure) compared to those with normal renal function.

Ezetimibe

No clinically significant differences in the pharmacokinetics of ezetimibe were observed in subjects with severe renal impairment compared to those with normal renal function.

Patients with Hepatic Impairment

NEXLIZET is not recommended in patients with moderate or severe hepatic impairment due to the unknown effects of the increased exposure to ezetimibe [see Use in Specific Populations (8.7)].

Bempedoic acid

No clinically significant differences in the pharmacokinetics of bempedoic acid and its metabolite (ESP15228) were observed in subjects with mild or moderate hepatic impairment (Child-Pugh A or B) compared to those with normal hepatic function. The effect of severe hepatic impairment (Child-Pugh C) on bempedoic acid pharmacokinetics is unknown.

Ezetimibe

After a single 10 mg dose of ezetimibe, the mean AUC for total ezetimibe increased approximately 1.7-fold in patients with mild hepatic impairment (Child-Pugh score 5 to 6), compared to healthy subjects. The mean AUC values for total ezetimibe and ezetimibe increased approximately 3- to 4-fold and 5- to 6-fold, respectively, in patients with moderate (Child-Pugh score 7 to 9) or severe hepatic impairment (Child-Pugh score 10 to 15). In a 14-day, multiple-dose study (10 mg daily) in patients with moderate hepatic impairment, the mean AUC for total ezetimibe and ezetimibe increased approximately 4-fold on day 1 and day 14 compared to healthy subjects.

Other Specific Populations

Bempedoic acid

The pharmacokinetics of bempedoic acid were not affected by age, gender, race, or weight.

Ezetimibe

Geriatrics: In a multiple-dose study with ezetimibe given 10 mg once daily for 10 days, plasma concentrations for total ezetimibe were about 2-fold higher in older (≥ 65 years) healthy subjects compared to younger subjects [see Use in Specific Populations (8.5)].

Gender: In a multiple-dose study with ezetimibe given 10 mg once daily for 10 days, plasma concentrations for total ezetimibe were slightly higher (<20%) in females than in males.

Race: The pharmacokinetics of ezetimibe is not affected by race.

Drug Interaction Studies

Bempedoic acid

Cytochrome P450 Substrates

In vitro metabolic interaction studies suggest that bempedoic acid, as well as its active metabolite and glucuronide forms are not metabolized by and do not interact with cytochrome P450 enzymes.

Transporter-mediated Drug Interactions

In vitro drug interaction studies suggest bempedoic acid, as well as its active metabolite and glucuronide form, are not substrates of commonly characterized drug transporters with the exception of bempedoic acid glucuronide, which is an OAT3 substrate. Bempedoic acid weakly inhibits OAT3 at high multiples of clinically relevant concentrations, and bempedoic acid and its glucuronide weakly inhibit OATP1B1, and OATP1B3 at clinically relevant concentrations. Bempedoic acid weakly inhibits OAT2 in vitro, which is likely the mechanism responsible for minor elevations in serum creatinine and uric acid [see Adverse Reactions (6.1)].

Probenecid

Administration of bempedoic acid 180 mg with steady-state probenecid resulted in a 1.7- and a 1.2-fold increase in bempedoic acid AUC and Cmax, respectively. AUC and Cmax for bempedoic acid active metabolite (ESP15228) were increased 1.9- and 1.5-fold, respectively. These elevations are not clinically meaningful and do not impact dosing recommendations.

Statins

The pharmacokinetic interactions between bempedoic acid (at systemic exposure relevant to the indicated CVD population) and simvastatin 20 mg, atorvastatin 10 mg, pravastatin 40 mg, and rosuvastatin 10 mg were evaluated in clinical trials.

Simvastatin: Administration of simvastatin 20 mg with 240 mg of bempedoic acid or 40 mg with 180 mg of bempedoic acid in healthy subjects at steady-state resulted in approximately 2-fold (91% for 20 mg and 96% for 40 mg) and 1.5-fold (54% for 20 mg and 52% for 40 mg) increases in simvastatin acid AUC and Cmax, respectively [see Drug Interactions (7)].

Pravastatin: Administration of pravastatin 40 mg with steady-state bempedoic acid 240 mg in healthy subjects resulted in 99% (2-fold) and 104% (2-fold) increases in pravastatin acid AUC and Cmax, respectively [see Drug Interactions (7)].

Atorvastatin and Rosuvastatin: Elevations of 1.7-fold in AUC of atorvastatin, and rosuvastatin and/or their major metabolites were observed, suggesting a weak interaction. These elevations were generally within the individual statin exposures and do not impact dosing recommendations.

Warfarin

In vitro studies indicate that bempedoic acid is not an inhibitor or inducer of CYP2C9. Because warfarin is primarily eliminated through CYP2C9, its pharmacokinetics is not expected to be altered by bempedoic acid.

Other

Bempedoic acid had no effect on the pharmacokinetics of metformin or the oral contraceptive Ortho-Novum 1/35.

Ezetimibe

Ezetimibe had no significant effect on a series of probe drugs (caffeine, dextromethorphan, tolbutamide, and IV midazolam) known to be metabolized by cytochrome P450 (1A2, 2D6, 2C8/9 and 3A4) in a "cocktail" study of twelve healthy adult males. This indicates that ezetimibe is neither an inhibitor nor an inducer of these cytochrome P450 isozymes, and it is unlikely that ezetimibe will affect the metabolism of drugs that are metabolized by these enzymes.

Cyclosporine: Administration of ezetimibe with cyclosporine (75–150 mg BID) resulted in a 2.4- and a 2.9-fold increase in total ezetimibe AUC and Cmax, respectively [see Drug Interactions (7)].

Fibrates: Administration of ezetimibe with fenofibrate (200 mg QD for 14 days) resulted in a 1.48- and a 1.64-fold increase in total ezetimibe AUC and Cmax, respectively. Administration with gemfibrozil (600 mg BID for 7 days) resulted in a 1.64- and 1.91-fold increase in total ezetimibe AUC and Cmax, respectively [see Drug Interactions (7)].

Cholestyramine: Administration of ezetimibe with cholestyramine (4 g BID for 14 days) resulted in a 55% and a 4% decrease in total ezetimibe AUC and Cmax, respectively [see Drug Interactions (7)].

No clinically meaningful pharmacokinetic interaction was observed following coadministration of ezetimibe with aluminum & magnesium hydroxide combination antacid, cimetidine, glipizide, lovastatin, pravastatin, atorvastatin, rosuvastatin, fluvastatin, simvastatin, digoxin, ethinyl estradiol/levonorgestrel, and warfarin.

13 NONCLINICAL TOXICOLOGY

13.1 Carcinogenesis, Mutagenesis, Impairment of Fertility

Bempedoic acid

Bempedoic acid was negative for mutagenicity in an in vitro Ames assay and negative for clastogenicity in the vitro human lymphocyte chromosome aberration assay. Bempedoic acid was negative in both in vivo mouse micronucleus and in vivo rat bone marrow micronucleus/liver comet assay. In a 2-year rat carcinogenicity study, Wistar rats were given oral doses of bempedoic acid at 3, 10 and 30 mg/kg/day. An increased incidence of liver hepatocellular adenomas and hepatocellular adenomas combined with carcinomas, thyroid gland follicular cell adenoma and follicular cell adenomas combined with carcinomas, and pancreatic islet cell adenomas combined with carcinomas were observed in male rats at the dose of 30 mg/kg/day (exposure equivalent to the maximum recommended human dose (MRHD), based on AUC). In a 2-year mice carcinogenicity study, CD-1 mice were given oral doses of bempedoic acid at 25, 75 and 150 mg/kg/day. Bempedoic acid-related increases in the incidence of liver hepatocellular adenomas, hepatocellular carcinomas and hepatocellular adenomas combined with carcinomas in male mice were observed at 75 and 150 mg/kg/day (exposures equivalent to the MRHD). Observations of liver and thyroid tumors are consistent with PPAR alpha agonism in rodents. The human relevance of pancreatic islet cell tumor findings is unknown.

In fertility and early embryofetal development study in rats, bempedoic acid was given orally to male and female rats at 10, 30 and 60 mg/kg/day. Males were dosed for 28 days prior to mating and females were dosed 14 days prior to mating through gestation day 7. No adverse effects on fertility were observed in females in the absence of maternal toxicity. No effects were observed on male fertility outcomes, but decreases in sperm counts were observed at 60 mg/kg/day (9 times the MRHD).

Ezetimibe

A 104-week dietary carcinogenicity study with ezetimibe was conducted in rats at doses up to 1,500 mg/kg/day (males) and 500 mg/kg/day (females) (approximately 20 times the human exposure at 10 mg daily based on AUC0-24hr for total ezetimibe). A 104-week dietary carcinogenicity study with ezetimibe was also conducted in mice at doses up to 500 mg/kg/day (>150 times the human exposure at 10 mg daily based on AUC0-24hr for total ezetimibe). There were no statistically significant increases in tumor incidences in drug-treated rats or mice.

No evidence of mutagenicity was observed in vitro in a microbial mutagenicity (Ames) test with Salmonella typhimurium and Escherichia coli with or without metabolic activation. No evidence of clastogenicity was observed in vitro in a chromosomal aberration assay in human peripheral blood lymphocytes with or without metabolic activation. In addition, there was no evidence of genotoxicity in the in vivo mouse micronucleus test.

In oral (gavage) fertility studies of ezetimibe conducted in rats, there was no evidence of reproductive toxicity at doses up to 1,000 mg/kg/day in male or female rats (approximately 7 times the human exposure at 10 mg daily based on AUC0-24hr for total ezetimibe).

14 CLINICAL STUDIES

14.1 Primary Hypercholesterolemia Trials in Adults

The efficacy of NEXLIZET was investigated in a single, multi-center, randomized, double-blind, placebo-controlled, parallel group trial that enrolled 301 patients with HeFH, established CVD, or multiple risk factors for CVD on maximally tolerated statin therapy.

Trial 1 (NCT03337308) was a 4-arm, 12-week trial that assessed the efficacy of NEXLIZET in 301 patients randomized 2:2:2:1 to receive either oral NEXLIZET (180 mg of bempedoic acid and 10 mg of ezetimibe) (n = 86), bempedoic acid 180 mg (n = 88), ezetimibe 10 mg (n = 86), or placebo (n = 41) once daily as add-on to maximally tolerated statin therapy. Patients were stratified by cardiovascular risk and baseline statin intensity. Patients on simvastatin 40 mg per day or higher and patients taking non-statin lipid-lowering therapy (including fibrates, niacin, bile acid sequestrants, ezetimibe, and PCSK9 inhibitors) were excluded from the trial.

Baseline Demographics and Disease Characteristics: Overall, the mean age at baseline was 64 years (range: 30 to 87 years), 50% were 65 years of age and older, 50% were female, 81% were White, 17% were Black or African American, 1% were Asian, and 1% were other races; 12% identified as Hispanic or Latino ethnicity. Sixty-two percent (62%) of patients had clinical CVD and/or a diagnosis of HeFH. The mean baseline LDL-C was 149.7 mg/dL. At the time of randomization, 65% of patients were receiving statin therapy; and 35% were receiving high intensity statin therapy.

Efficacy Results: The primary efficacy outcome measure of the study was the percent change from baseline to Week 12 in LDL-C. The difference between NEXLIZET and placebo in mean percent change in LDL-C from baseline to Week 12 was -38% (95% CI: -47%, -30%; p <0.001). High-density lipoprotein (HDL) and triglycerides (TG) were examined as exploratory endpoints and were not included in the statistical hierarchy. The difference between NEXLIZET and placebo in mean percent change from baseline to Week 12 was -5% for HDL and median percent change from baseline to Week 12 was -11% for TG. The maximum LDL-C lowering effect was observed at Week 4. For additional results see Table 5.

Table 5. Lipid Parameters in Adult Patients with HeFH, CVD or Risk Factors for CVD on Maximally Tolerated Statin Therapy (Mean % Change from Baseline to Week 12 in Trial 1) [a. 3.5% of subjects on NEXLIZET, 6.8% of subjects on bempedoic acid, 7% of subjects on ezetimibe and 2.4% of subjects on placebo had missing LDL-C data at Week 12. Percent change from baseline was analyzed using analysis of covariance (ANCOVA), with treatment and randomization strata (high intensity statin versus other and CVD and/or HeFH versus multiple CV risk factors) as factors and baseline lipid parameter as a covariate. Missing data for LDL-C, non-HDL-C, TC and apo B were imputed through multiple imputation using a pattern mixture model (PMM) account for treatment adherence.]
 | LDL-C LS Mean | non-HDL-C LS Mean | apo B LS Mean | TC LS Mean
NEXLIZET (180 mg/10 mg; n = 86 [Number of randomized subjects at baseline]) | -36 | -32 | -25 | -26
Bempedoic acid (180 mg; n = 88) | -17 | -14 | -12 | -12
Ezetimibe (10 mg; n = 86) | -23 | -20 | -15 | -16
Placebo (n = 41) | 2 | 2 | 6 | 1
Mean Difference of NEXLIZET versus Placebo (95% CI) | -38 (-47, -30) | -34 (-44, -23) | -30 (-40, -20) | -27 (-35, -19)
apo B = apolipoprotein B; HDL-C = high-density lipoprotein cholesterol, LDL-C = low-density lipoprotein cholesterol; LS = least squares; SE = standard error; TC = total cholesterol.
Background statin: atorvastatin, lovastatin, pitavastatin, pravastatin, rosuvastatin, simvastatin.

Examination of age, sex, and race subgroups did not identify differences in response to NEXLIZET among these subgroups in any of the trials.

Bempedoic Acid

Primary Hypercholesterolemia

In the two primary hypercholesterolemia (52-week) trials (Trials 2 and 3) that included 3,009 adult patients with HeFH or established CVD on maximally tolerated statin therapy, the difference between bempedoic acid and placebo in mean percent change in LDL-C from baseline to Week 12 was -17% to -18%. Bempedoic acid also significantly lowered non-HDL-C (-13%), apo B (-12% to -13%), and TC (-11%) compared with placebo.

Ezetimibe

Ezetimibe Added to On-going Statin Therapy: In a multicenter, double-blind, placebo-controlled, 8-week trial, 769 patients (age range 22 to 85 years, 42% were females; 90% were White, 6% were Black or African American, 1% were Asian, and 3% were other races; 2% identified as Hispanic or Latino ethnicity) with primary hypercholesterolemia, known coronary heart disease or multiple cardiovascular risk factors who were already receiving statin monotherapy, but who had not met their NCEP ATP II target LDL-C goal, were randomized to receive either ezetimibe or placebo in addition to their on-going statin therapy.

Ezetimibe, added to on-going statin therapy, significantly lowered TC (-17%), LDL-C (-25%), apo B (-19%), and non-HDL-C (-23%) relative to baseline and compared with a statin administered alone. LDL-C reductions induced by ezetimibe were generally consistent across all statins.

Ezetimibe Initiated Concurrently with a Statin: In four, multicenter, double-blind, placebo-controlled, 12-week trials, in 2,382 patients (age range 18 to 87 years, 57% were female; 88% were White, 5% were Black or African American, 2% were Asian, and 5% were other races mostly identified as Hispanic or Latino ethnicity) with hypercholesterolemia, ezetimibe or placebo was orally administered alone or with various doses of atorvastatin, simvastatin, pravastatin, or lovastatin. When all patients receiving ezetimibe with a statin were compared to all those receiving the corresponding statin alone, ezetimibe significantly lowered LDL-C (ezetimibe + all atorvastatin doses [-56%] versus all atorvastatin doses alone [-44%]; ezetimibe + all simvastatin doses [-51%] versus all simvastatin doses alone [-36%]; ezetimibe + all pravastatin doses [-39%] versus all pravastatin doses alone [-25%]; ezetimibe + all lovastatin doses [-40%] versus all lovastatin doses alone [-25%]). LDL-C reductions induced by ezetimibe were generally consistent across all statins.

14.2 Cardiovascular Outcomes Trial in Adults With CVD or at High Risk for CVD

Trial 4 (NCT02993406) was a randomized, double-blind, placebo-controlled, event-driven trial in 13,970 adult patients with established CVD (70%) or at high risk for a CVD event but without CVD (30%) who were not receiving recommended statin dosages. Patients with established CVD had documented history of coronary artery disease, symptomatic peripheral arterial disease, and/or cerebrovascular atherosclerotic disease. Patients without established CVD were considered at high risk for CVD based on meeting at least one of the following criteria:

(1) Diabetes mellitus (type 1 or type 2) in females over 65 years of age or males over 60 years of age;
  (2) A Reynolds Risk score > 30% or a SCORE Risk score > 7.5% over 10 years. Reynolds risk score and SCORE risk score evaluate a 10-year risk of having a cardiovascular (CV) event. The Reynolds risk score is based on the following risk factors: sex, age, smoking status, systolic blood pressure, total cholesterol, HDL cholesterol, high sensitivity C-reactive protein (hsCRP), and familial history of CVD events. LDL-C is an additional risk factor considered in SCORE risk score; or
  (3) A coronary artery calcium score >400 Agatston units at any time in the past.

Patients were randomized 1:1 to receive either oral bempedoic acid 180 mg per day (n = 6,992) or placebo (n = 6,978), alone or as an add on to other background lipid-lowering therapies. Background therapy could include less than low-intensity statin dosages. Overall, 95.3% of adult patients were followed until the end of the trial or death. The median follow-up duration was 3.4 years.

Baseline Demographics and Disease Characteristics

At baseline, the mean age was 66 years (range 21 to 92 years), 59% were 65 years of age and older, 15% were 75 years of age and older, 48% were female, 91% were White, 2% were Black or African American, 4% were American Indian or Alaska Native, 2% were Asian, and 1% were other races; 17% identified as Hispanic or Latino ethnicity.

Selected additional baseline characteristics included hypertension (85%), diabetes mellitus (46%), current tobacco user (22%), eGFR < 60 mL/min per 1.73 m^2 (21%), and a mean body mass index of 30 kg/m^2. The mean baseline LDL-C was 139 mg/dL. At baseline, 38% of patients were taking at least one lipid modifying therapy including less than low-intensity statin dosages (23%), ezetimibe (12%), or fibrates (5%). Most patients were taking at least one other CV medication including acetylsalicylic acid (57%), selective beta blockers (52%), angiotensin converting enzyme inhibitors (40%), or angiotensin receptor blockers (32%).

Efficacy Results

The risk for the primary composite endpoint (MACE-4: time to first occurrence of CV death, nonfatal myocardial infarction, nonfatal stroke, or coronary revascularization; p= 0.0037) and the key secondary composite endpoint (MACE-3: time to first occurrence of CV death, nonfatal myocardial infarction, or nonfatal stroke; p= 0.0058) was significantly reduced in bempedoic acid-treated patients compared to the placebo-treated patients (Table 6). The difference between bempedoic acid and placebo in mean percent change in LDL-C from baseline to Month 6 was -20% (95% CI: -21%, -19%).

Table 6: Major Cardiovascular Events in Adults with Established CVD or at High Risk for CVD (Trial 4)
Endpoint | Bempedoic acid N=6,992 | Placebo N=6,978 | Bempedoic acid vs. Placebo
Endpoint | n (%) | n (%) | Hazard Ratio (95% CI)
Primary Composite Endpoint
Cardiovascular death, non-fatal myocardial infarction, non-fatal stroke, coronary revascularization (MACE-4) | 819 (11.7) | 927 (13.3) | 0.87 (0.79, 0.96)
Key Secondary Endpoint
Cardiovascular death, non-fatal myocardial infarction, non-fatal stroke (MACE-3) | 575 (8.2) | 663 (9.5) | 0.85 (0.76, 0.96)
Components of Primary Composite Endpoint
Non-fatal myocardial infarction | 236 (3.4) | 317 (4.5) | 0.73 (0.62, 0.87)
Coronary revascularization | 435 (6.2) | 529 (7.6) | 0.81 (0.72, 0.92)
Non-fatal stroke | 119 (1.7) | 144 (2.1) | 0.82 (0.64, 1.05)
Cardiovascular death | 269 (3.8) | 257 (3.7) | 1.04 (0.88, 1.24)
CI = confidence interval; MACE = major adverse cardiac event.
aHazard ratio and corresponding 95% CI were based on a Cox proportional hazard model fitting treatment as explanatory variable.
This table also presents the time to first occurrence for each of the components of MACE; patients may have been included in more than one category.

The Kaplan-Meier estimates of the cumulative incidence of the MACE-4 and MACE-3 endpoints are shown in Figure 1 and 2 below.

Figure 1: Cumulative Incidence of Primary Composite Endpoint (MACE-4) Over 4.5 Years in Adults with Established CVD or at High Risk for CVD (Trial 4)

MACE = major adverse cardiac event
Note: MACE-4 was defined as the time to first occurrence of the composite endpoint of CV death, nonfatal MI, nonfatal stroke, or coronary revascularization.

Figure 2: Cumulative Incidence of Composite Endpoint (MACE-3) Over 4.5 Years in Adults with Established CVD or at High Risk for CVD (Trial 4)

MACE = major adverse cardiac event
MACE-3 was defined as time to first occurrence of the composite endpoint of CV death, nonfatal MI, or nonfatal stroke.

16 HOW SUPPLIED/STORAGE AND HANDLING

How Supplied

NEXLIZET tablets are supplied as follows:

Tablet Strength | Description | Package Configuration | NDC No.
180 mg of bempedoic acid and 10 mg of ezetimibe | blue, oval shaped, debossed with "818" on one side and "ESP" on the other side | Bottle of 30 tablets with child-resistant cap | 72426-818-03

Storage and Handling

Store at 68°F to 77°F (20°C to 25°C); excursions permitted to 59°F to 86°F (15°C to 30°C) [see USP Controlled Room Temperature]. Store and dispense in the original package protected from extreme heat and humidity. Do not discard desiccant.

17 PATIENT COUNSELING INFORMATION

Advise patients to read the FDA-approved patient labeling (Patient Information).

Risk of Hyperuricemia

Advise patients of the risk of elevated serum uric acid levels, including development of gout. Inform patients that serum uric acid levels may be monitored during treatment with NEXLIZET. Patients with signs or symptoms of hyperuricemia should contact their healthcare provider if symptoms occur [see Warnings and Precautions (5.1)].

Risk of Tendon Rupture

Inform patients of the risk of tendon rupture. Advise patients to rest at the first sign of tendinitis or tendon rupture and to immediately contact their healthcare provider if tendinitis or tendon rupture symptoms occur [see Warnings and Precautions (5.2)].

Risk of Myopathy with Concomitant Use of Simvastatin or Pravastatin

Advise patients to notify their healthcare provider(s) if they are taking, or plan to take simvastatin or pravastatin. The risk of myopathy occurring with the use of simvastatin or pravastatin may be increased when taken with NEXLIZET [see Drug Interactions (7)].

Pregnancy

Advise pregnant women of the potential risk to a fetus based on NEXLIZET's mechanism of action. Advise females to inform their healthcare provider of a known or suspected pregnancy. Advise patients that there is a pregnancy safety study that monitors pregnancy outcomes in patients exposed to NEXLIZET during pregnancy. Encourage these patients to report their pregnancy to Esperion at 1-833-377-7633 [see Use in Specific Populations (8.1)].

Manufactured for:
Esperion Therapeutics, Inc.
3891 Ranchero Drive, Suite 150
Ann Arbor, MI 48108

NEXLIZET® (bempedoic acid and ezetimibe)
© 2026 Esperion Therapeutics, Inc.

PATIENT INFORMATION
NEXLIZET® (NEX-lee-zet)
(bempedoic acid and ezetimibe)
tablets, for oral use

What is NEXLIZET?
NEXLIZET is a prescription medicine that contains 2 cholesterol-lowering medicines, bempedoic acid and ezetimibe.

- NEXLIZET is used along with diet and exercise to reduce low-density lipoprotein (LDL, or bad cholesterol) in adults with high blood cholesterol levels called hypercholesterolemia, including a type of high cholesterol called heterozygous familial hypercholesterolemia (HeFH).
- Bempedoic acid, a component of NEXLIZET, is used:
  - to lower the risk of major adverse cardiovascular (CV) events, such as death from cardiovascular disease, heart attack, stroke, or heart procedures like stent placement or bypass surgery in adults at increased risk for these events who are unable to take recommended statin treatment (a cholesterol-lowering medicine), or are not taking a statin

It is not known if NEXLIZET is safe and effective in children.

Do not take NEXLIZET if you are allergic to ezetimibe, bempedoic acid, or any of the ingredients in NEXLIZET. See the end of this leaflet for a complete list of ingredients in NEXLIZET. Stop taking NEXLIZET, call your healthcare provider or go to the nearest hospital emergency room right away if you have any signs or symptoms of an allergic reaction including:

- swelling of your face, lips, mouth or tongue
- wheezing
- severe itching
- fast heart beat or pounding in your chest

- trouble breathing
- skin rashes, redness, or swelling
- dizziness or fainting

Before you start taking NEXLIZET, tell your healthcare provider about all your medical conditions, including if you:

- have or had gout.
- have or had tendon problems.
- are pregnant or think you may be pregnant. Tell your healthcare provider right away if you become pregnant while taking NEXLIZET. You and your healthcare provider will decide if you should take NEXLIZET while you are pregnant. If you are pregnant during NEXLIZET treatment, you are encouraged to call Esperion at 1-833-377-7633 to share information about the health of you and your baby.
- are breastfeeding or plan to breastfeed. NEXLIZET may pass into your breastmilk. You and your healthcare provider should decide if you will take NEXLIZET or breastfeed.
- have moderate or severe liver problems.

NEXLIZET may affect the way other medicines work, and other medicines may affect how NEXLIZET works. Tell your healthcare provider about all the medicines you take, including prescription and over-the-counter medicines, vitamins, and herbal supplements.
Especially tell your healthcare provider if you take or plan to take:

- simvastatin or pravastatin (other cholesterol-lowering medicines). Taking simvastatin or pravastatin with NEXLIZET may increase your risk of developing muscle pain or weakness (myopathy).
- cyclosporine (often used in organ transplant patients)
- fibrates (triglyceride-lowering medicines). Taking a fibrate medicine with NEXLIZET may lead to increases in triglycerides (fat in the blood) and decreases in high-density lipoprotein (HDL, good cholesterol).
- cholestyramine (used to lower cholesterol)

Know the medicines you take. Keep a list of them to show your healthcare provider and pharmacist when you get a new medicine.

How should I take NEXLIZET?

- Take NEXLIZET exactly as your healthcare provider tells you to take it. Check with your healthcare provider or pharmacist if you are not sure.
- Take 1 NEXLIZET tablet by mouth each day.
- Swallow the NEXLIZET tablet whole. Do not cut, chew, or crush the tablet.
- You may take NEXLIZET with or without food.
- If you miss a dose, take it as soon as you remember. If you do not remember until it is time for your next dose, skip the missed dose and go back to your regular schedule. Do not take 2 doses of NEXLIZET at the same time.
- If you take a medicine that lowers cholesterol by binding bile acids, such as colesevelam or cholestyramine, take NEXLIZET at least 2 hours before or 4 hours after you take bile acid binding medicines. Ask your healthcare provider if you are not sure if you take these medicines.
- Your healthcare provider may do blood tests to check your LDL-C levels between 8 to 12 weeks after starting treatment with NEXLIZET.
- In case of an overdose, get medical help or contact a live Poison Center expert right away at 1-800-222-1222. Advice is also available online at poisonhelp.org.

What are possible side effects of NEXLIZET?
NEXLIZET may cause serious side effects, including:

- increased levels of uric acid in your blood (hyperuricemia). This can happen within 4 weeks of you starting NEXLIZET and continue throughout your treatment. Your healthcare provider may monitor your blood uric acid levels while you are taking NEXLIZET. High levels of blood uric acid may lead to gout. Call your healthcare provider if you have the following symptoms of hyperuricemia and gout:

- severe foot pain especially in the toe joint
- warm joints
- swelling

- tender joints
- joint redness

- tendon rupture or injury. Tendon problems can happen in people who take bempedoic acid, one of the medicines in NEXLIZET. Tendons are tough cords of tissue that connect muscles to bones. Symptoms of tendon problems may include pain, swelling, tears, and inflammation of tendons, most commonly with the rotator cuff (the shoulder), the biceps tendon (upper arm), and Achilles tendon at the back of the ankle. This can also happen with other tendons. Tendon ruptures can happen within weeks or months of starting NEXLIZET.
  - The risk of getting tendon problems while you take NEXLIZET is higher if you:

- are over 60 years of age
- are taking antibiotics (fluoroquinolones)
- have had tendon problems

- are taking steroids (corticosteroids)
- have renal failure

- Stop taking NEXLIZET immediately and get medical help right away if you get any of the following signs or symptoms of a tendon rupture:
  - hear or feel a snap or pop in a tendon area
  - bruising right after an injury in a tendon area
  - unable to move the affected area or put weight on the affected area
  Avoid exercise and using the affected area.

The most common side effects of NEXLIZET in people with primary hypercholesterolemia include:

- symptoms of the common cold, flu, or flu-like symptoms
- muscle spasms
- back pain
- stomach pain
- bronchitis
- pain in shoulder, legs, or arms

- anemia
- increased liver enzymes
- diarrhea
- joint pain
- swelling of sinuses (sinusitis)
- fatigue

The most common side effects of bempedoic acid in people with heart problems include:

- kidney problems
- anemia
- increased liver enzymes

- muscle spasms
- gallstones

Tell your healthcare provider if you have any side effect that bothers you or that does not go away.
These are not all the possible side effects of NEXLIZET. Ask your healthcare provider or pharmacist for more information.
Call your doctor for medical advice about side effects. You may report side effects to FDA at 1-800-FDA-1088.

How should I store NEXLIZET?

- Store NEXLIZET in the original package at room temperature between 68ºF to 77ºF (20ºC to 25ºC).
- Protect from heat and moisture.
- Do not throw away the packet that helps to keep your medicine dry (desiccant).
- NEXLIZET comes in a bottle with a child-resistant cap.

Keep NEXLIZET and all medicines out of the reach of children.

General information about the safe and effective use of NEXLIZET.
Medicines are sometimes prescribed for purposes other than those listed in a Patient Information leaflet. Do not use NEXLIZET for a condition for which it was not prescribed. Do not give NEXLIZET to other people, even if they have the same symptoms that you have. It may harm them.
You can ask your pharmacist or healthcare provider for information about NEXLIZET that is written for healthcare professionals.

What are the ingredients in NEXLIZET?

- active ingredients: bempedoic acid and ezetimibe
- inactive ingredients: colloidal silicon dioxide, hydroxy propyl cellulose, lactose monohydrate, magnesium stearate, microcrystalline cellulose, povidone K30, sodium lauryl sulfate, sodium starch glycolate
- tablet coating: FD&C Blue #1/Brilliant Blue FCF Aluminum Lake, FD&C Blue #2/Indigo Carmine Aluminum Lake, glyceryl monocaprylocaprate, partially hydrolyzed polyvinyl alcohol, sodium lauryl sulfate, talc, and titanium dioxide

Manufactured for:
Esperion Therapeutics, Inc.
3891 Ranchero Drive, Suite 150
Ann Arbor, MI 48108
© 2026 Esperion Therapeutics, Inc.

This Patient Information has been approved by the U.S. Food and Drug Administration

Revised: 01/2026

PRINCIPAL DISPLAY PANEL - 180 mg/10 mg Tablet Bottle Label

NDC 72426-818-03
Rx only

NEXLIZET®
(bempedoic acid
and ezetimibe) tablets

Contains
30 Tablets

180 mg/10 mg